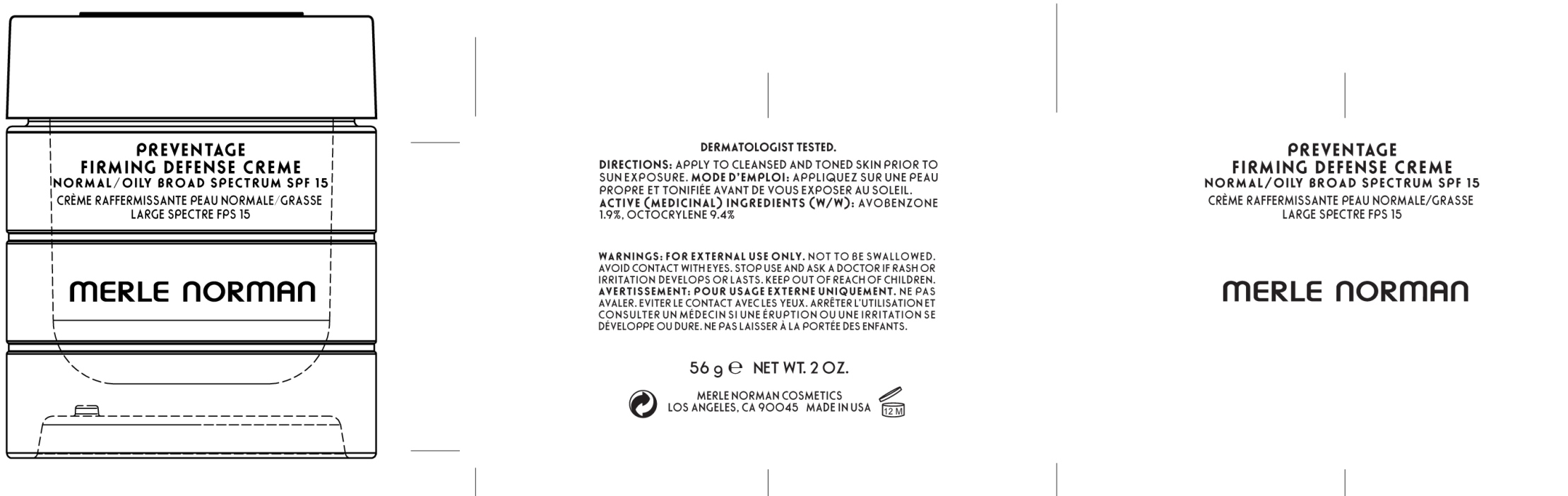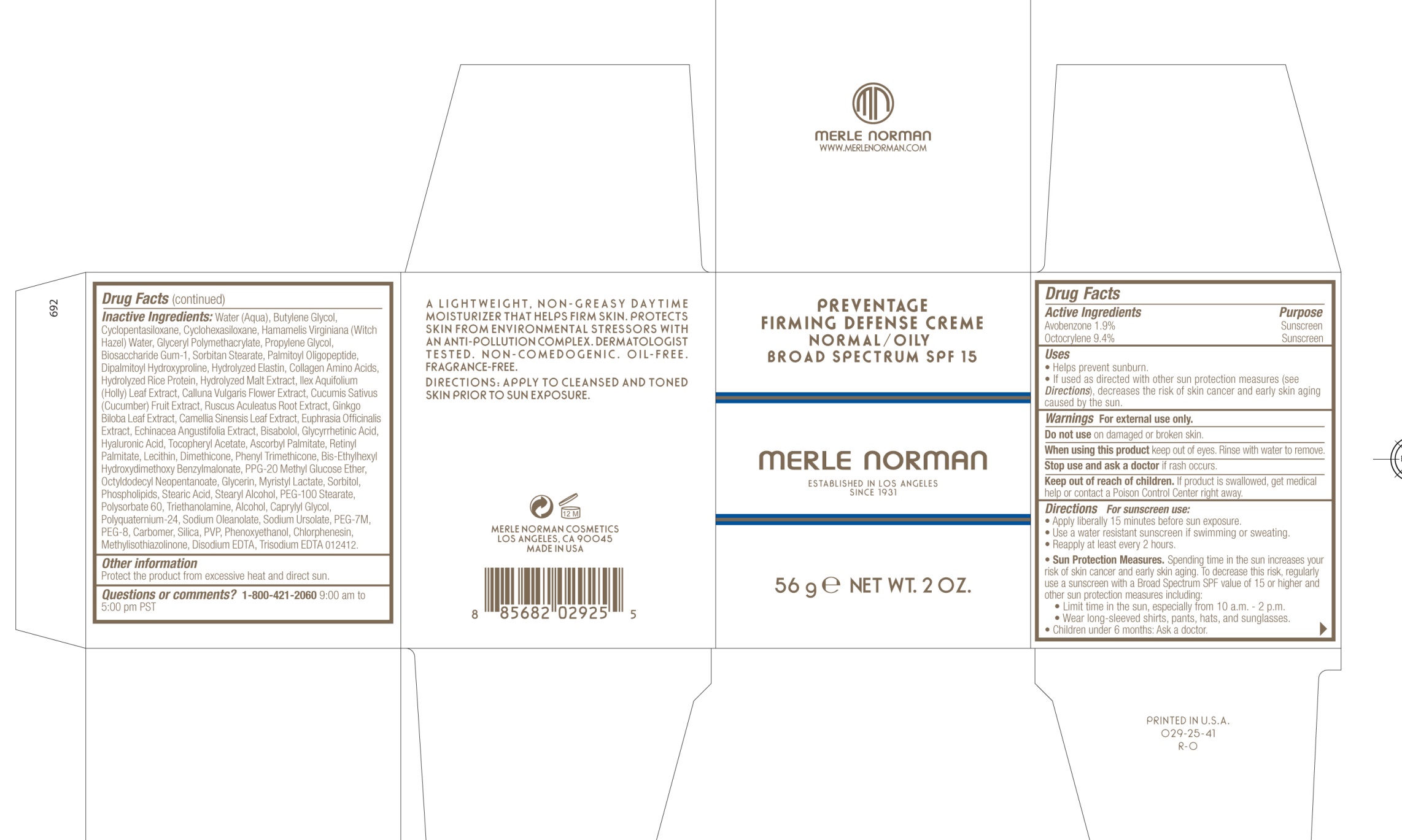 DRUG LABEL: Preventage Firming Defense Normal/Oily Broad Spectrum SPF 15
NDC: 57627-119 | Form: CREAM
Manufacturer: Merle Norman Cosmetics, Inc 
Category: otc | Type: HUMAN OTC DRUG LABEL
Date: 20200127

ACTIVE INGREDIENTS: AVOBENZONE 1.064 g/56 g; OCTOCRYLENE 5.264 g/56 g
INACTIVE INGREDIENTS: WATER; BUTYLENE GLYCOL; CYCLOMETHICONE 5; CYCLOMETHICONE 6; HAMAMELIS VIRGINIANA TOP WATER; PROPYLENE GLYCOL; BIOSACCHARIDE GUM-1; SORBITAN MONOSTEARATE; PALMITOYL OLIGOPEPTIDE; DIPALMITOYL HYDROXYPROLINE; HYDROLYZED ELASTIN, BOVINE, ALKALINE (1000 MW); ILEX AQUIFOLIUM LEAF; CALLUNA VULGARIS FLOWERING TOP; CUCUMBER; RUSCUS ACULEATUS ROOT; GINKGO; GREEN TEA LEAF; EUPHRASIA STRICTA; ECHINACEA ANGUSTIFOLIA; LEVOMENOL; ENOXOLONE; HYALURONIC ACID; .ALPHA.-TOCOPHEROL ACETATE; ASCORBYL PALMITATE; VITAMIN A PALMITATE; DIMETHICONE; PHENYL TRIMETHICONE; BIS-ETHYLHEXYL HYDROXYDIMETHOXY BENZYLMALONATE; PPG-20 METHYL GLUCOSE ETHER; OCTYLDODECYL NEOPENTANOATE; GLYCERIN; MYRISTYL LACTATE; SORBITOL; STEARIC ACID; STEARYL ALCOHOL; PEG-100 STEARATE; POLYSORBATE 60; TROLAMINE; ALCOHOL; CAPRYLYL GLYCOL; SODIUM OLEANOLATE; SODIUM URSOLATE; POLYETHYLENE GLYCOL 300000; POLYETHYLENE GLYCOL 400; SILICON DIOXIDE; PHENOXYETHANOL; CHLORPHENESIN; METHYLISOTHIAZOLINONE; EDETATE DISODIUM; EDETATE TRISODIUM

Merle Norman Preventage Defense Cream Normal Oily SPF 15

Active Ingredients Purpose

Avobenzone 1.9% Sunscreen

Octocrylene 9.4% Sunscreen

Uses

-Helps prevent sunburn

-If used as directed with other sun protection measures (see Directions), decreases the risk of skin cancer and early skin aging caused by the sun.

Keep out of reach of children. If product is swallowed, get medical help or contact a Poison Control Center right away.

Stop use and ask a doctor if rash occurs.

Warnings

For external use only.

Do not use on damaged or broken skin.

When using this product keep out of eyes. Rinse with water to remove.

DOSAGE AND ADMINISTRATION

Directions For sunscreen use:

Apply liberally 15 minutes before sun exposure.

Use a water resistant sunscreen if swimming or sweating.

Reapply at least every 2 hours.

Sun Protection Measures. Spending time in the sun increases your risk of skin cancer and early skin aging. To decrease this risk, regularly use a sunscreen with a Broad Spectrum SPF value of 15 or higher and other sun protection measures including:

Limit time in the sun, especially from 10 a.m. – 2 p.m.

Wear long-sleeved shirts, pants, hats, and sunglasses.

Children under 6 months: Ask a doctor.

INACTIVE INGREDIENT

Inactive ingredients: Water(Aqua), Butylene Glycol, Cyclopentasiloxane, Cyclohexasiloxane, Hamamelis Virginiana (Witch Hazel) Water, Glyceryl Polymethacrylate, Propylene Glycol, Biosaccharide Gum-1, Sorbitan Stearate, Palmitoyl Oligopeptide, Dipalmitoyl Hydroxyproline, Hydrolyzed Elastin, Collagen Amino Acids, Hydrolyzed Rice Protein, Hydrolyzed Malt Extract, Ilex Aquifolium (Holly) Leaf Extract, Calluna Vulgaris Flower Extract, Cucumis Sativus (Cucumber) Fruit Extract, Ruscus Aculeatus Root Extract, Ginkgo Biloba Leaf Extract, Camellia Sinensis Leaf Extract, Euphrasia Officinalis Extract, Echinacea Angustifolia Extract, Bisabolol, Glycyrrhetinic Acid, Hyaluronic Acid, Tocopheryl Acetate, Ascorbyl Palmitate, Retinyl Palmitate, Lecithin, Dimethicone, Phenyl Trimethicone, Bis-Ethylhexyl Hydroxydimethoxy Benzylmalonate, PPG-20 Methyl Glucose Ether, Octyldodecyl Neopentanoate, Glycerin, Myristyl Lactate, Sorbitol, Phospholipids, Stearic Acid, Stearyl Alcohol, PEG-100 Stearate, Polysorbate 60, Triethanolamine, Alcohol, Caprylyl Glycol, Polyquaternium-24, Sodium Oleanolate, Sodium Ursolate, PEG-7M, PEG-8, Carbomer, Silica, PVP, Phenoxyethanol, Chlorphenesin, Methylisothiazolinone, Disodium EDTA, Trisodium EDTA

PACKAGE LABEL

Merle Norman Preventage Defense Cream Normal Oily SPF 15

Merle Norman

Established in Los Angeles in 1931

56 g Net Wt 2 oz